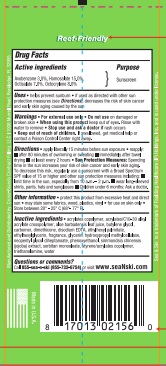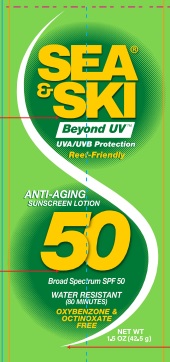 DRUG LABEL: Sea and Ski SPF 50
NDC: 73440-2156 | Form: LOTION
Manufacturer: Cross Brands Contract Filling
Category: otc | Type: HUMAN OTC DRUG LABEL
Date: 20210219

ACTIVE INGREDIENTS: AVOBENZONE 1.275 g/42.5 g; HOMOSALATE 6.375 g/42.5 g; OCTISALATE 2.975 g/42.5 g; OCTOCRYLENE 3.4 g/42.5 g
INACTIVE INGREDIENTS: WATER 19.95 g/42.5 g

Sea & Ski Reef-Friendly SPF 50 Lotion 1.5oz

Active ingredients

Avobenzone 3.0%, Homsalate 15.0%, Octisalate 7.0%, Octocrylene 8.0%

Purpose

Sunscreen

Uses

helps prevent sunburn. if used as directed with other sun protection measures (see Directions), decreases the risk of skin cancer and early skin aging caused by the sun

Warnings

For External Use Only

Do Not Use

on damaged or broken skin.

When Using this product

keep out of eyes. Rinse with water to remove

Stop Use and ask a doctor if

rash occurs

Keep out of reach of children

If swallowed, get medical help or contact a Poison Control Center right away.

Directions

apply liberally 15 minutes before sun exposure. reapply:

after 80 minutes of swimming or sweting

immediately after towl drying

at least every 2 hours

Sun Protection Measures:

Spending time in the sun increases your risk of skin cancer and early skin aging. To decrease this risk, regularly use a sunscreen with a Broad Spectrum SPF value of 15 or higher and other sun protection measures including:

Limit time in the sun, especially from 10 a.m. - 2 p. m.

wear long-sleeved shirts, pants, hats and sunglasses

Children under 6 months: Ask a doctor.

Other Information

protect this product from excessive heat and direct sun

may stain some fabrics, wood, plastics, vinyl

for use on skin only

store between 20°-25°C (68°-77°F).

Inactive ingredients

acrylates copolymer, acrylates/c10-30 alkyl acrylate crosspolymer, aloe barbadensis leaf juice, butylene glycol, carbomer, dimethicone, disodium EDTA, ethylhexyl palmitate, ethylhexylglycerin, fragrance, glycerin, hydroxypropyl methylcellulose, neopentyl glycol diheptanoate, phenoxyethanol, simmondsia chinensis (jojoba) extract, sorbitan monooleate, styrene/ acrylates

Questions or comments?

Call 855-sea-n-ski (855-732-6754) or visit www. seaNski.com